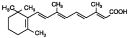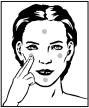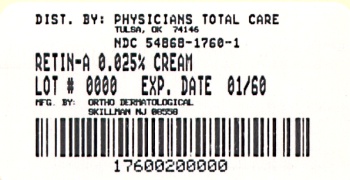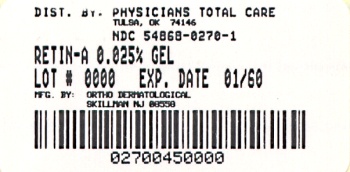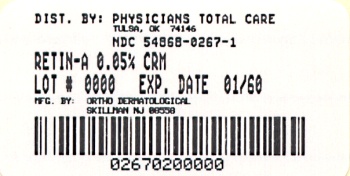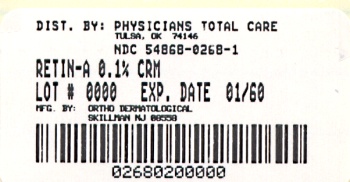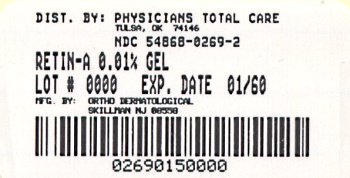 DRUG LABEL: Retin-A
NDC: 54868-1760 | Form: CREAM
Manufacturer: Physicians Total Care, Inc.
Category: prescription | Type: HUMAN PRESCRIPTION DRUG LABEL
Date: 20100427

ACTIVE INGREDIENTS: TRETINOIN 0.25 mg/1 g
INACTIVE INGREDIENTS: STEARIC ACID; ISOPROPYL MYRISTATE; POLYOXYL 40 STEARATE; STEARYL ALCOHOL; XANTHAN GUM; SORBIC ACID; BUTYLATED HYDROXYTOLUENE; WATER

For Topical Use Only

DESCRIPTION

RETIN-A Gel, Cream and Liquid, containing tretinoin are used for the topical treatment of acne vulgaris. RETIN-A Gel contains tretinoin (retinoic acid, vitamin A acid) in either of two strengths, 0.025% or 0.01% by weight, in a gel vehicle of butylated hydroxytoluene, hydroxypropyl cellulose and alcohol (denatured with tert-butyl alcohol and brucine sulfate) 90% w/w. RETIN-A (tretinoin) Cream contains tretinoin in either of three strengths, 0.1%, 0.05%, or 0.025% by weight, in a hydrophilic cream vehicle of stearic acid, isopropyl myristate, polyoxyl 40 stearate, stearyl alcohol, xanthan gum, sorbic acid, butylated hydroxytoluene, and purified water. RETIN-A Liquid contains tretinoin 0.05% by weight, polyethylene glycol 400, butylated hydroxytoluene and alcohol (denatured with tert-butyl alcohol and brucine sulfate) 55%. Chemically, tretinoin is all-trans-retinoic acid and has the following structure:

CLINICAL PHARMACOLOGY

Although the exact mode of action of tretinoin is unknown, current evidence suggests that topical tretinoin decreases cohesiveness of follicular epithelial cells with decreased microcomedo formation. Additionally, tretinoin stimulates mitotic activity and increased turnover of follicular epithelial cells causing extrusion of the comedones.

INDICATIONS AND USAGE

RETIN-A is indicated for topical application in the treatment of acne vulgaris. The safety and efficacy of the long-term use of this product in the treatment of other disorders have not been established.

CONTRAINDICATIONS

Use of the product should be discontinued if hypersensitivity to any of the ingredients is noted.

PRECAUTIONS

General: If a reaction suggesting sensitivity or chemical irritation occurs, use of the medication should be discontinued. Exposure to sunlight, including sunlamps, should be minimized during the use of RETIN-A, and patients with sunburn should be advised not to use the product until fully recovered because of heightened susceptibility to sunlight as a result of the use of tretinoin. Patients who may be required to have considerable sun exposure due to occupation and those with inherent sensitivity to the sun should exercise particular caution. Use of sunscreen products and protective clothing over treated areas is recommended when exposure cannot be avoided. Weather extremes, such as wind or cold, also may be irritating to patients under treatment with tretinoin.

RETIN-A (tretinoin) acne treatment should be kept away from the eyes, the mouth, angles of the nose, and mucous membranes. Topical use may induce severe local erythema and peeling at the site of application. If the degree of local irritation warrants, patients should be directed to use the medication less frequently, discontinue use temporarily, or discontinue use altogether. Tretinoin has been reported to cause severe irritation on eczematous skin and should be used with utmost caution in patients with this condition.

Drug Interactions: Concomitant topical medication, medicated or abrasive soaps and cleansers, soaps and cosmetics that have a strong drying effect, and products with high concentrations of alcohol, astringents, spices or lime should be used with caution because of possible interaction with tretinoin. Particular caution should be exercised in using preparations containing sulfur, resorcinol, or salicylic acid with RETIN-A. It also is advisable to “rest” a patient's skin until the effects of such preparations subside before use of RETIN-A is begun.

Carcinogenesis: Long-term animal studies to determine the carcinogenic potential of tretinoin have not been performed. Studies in hairless albino mice suggest that tretinoin may accelerate the tumorigenic potential of weakly carcinogenic light from a solar simulator. In other studies, when lightly pigmented hairless mice treated with tretinoin were exposed to carcinogenic doses of UVB light, the incidence and rate of development of skin tumors was reduced. Due to significantly different experimental conditions, no strict comparison of these disparate data is possible. Although the significance of these studies to man is not clear, patients should avoid or minimize exposure to sun.

Pregnancy: Teratogenic effects. Pregnancy Category C. Oral tretinoin has been shown to be teratogenic in rats when given in doses 1000 times the topical human dose. Oral tretinoin has been shown to be fetotoxic in rats when given in doses 500 times the topical human dose.

Topical tretinoin has not been shown to be teratogenic in rats and rabbits when given in doses of 100 and 320 times the topical human dose, respectively (assuming a 50 kg adult applies 250 mg of 0.1% cream topically). However, at these topical doses, delayed ossification of a number of bones occurred in both species. These changes may be considered variants of normal development and are usually corrected after weaning. There are no adequate and well-controlled studies in pregnant women. Tretinoin should be used during pregnancy only if the potential benefit justifies the potential risk to the fetus.

Nursing Mothers: It is not known whether this drug is excreted in human milk. Because many drugs are excreted in human milk, caution should be exercised when RETIN-A is administered to a nursing woman.

GELS ARE FLAMMABLE. Note: Keep away from heat and flame. Keep tube tightly closed.

ADVERSE REACTIONS

The skin of certain sensitive individuals may become excessively red, edematous, blistered, or crusted. If these effects occur, the medication should either be discontinued until the integrity of the skin is restored, or the medication should be adjusted to a level the patient can tolerate. True contact allergy to topical tretinoin is rarely encountered. Temporary hyper or hypopigmentation has been reported with repeated application of RETIN-A. Some individuals have been reported to have heightened susceptibility to sunlight while under treatment with RETIN-A. To date, all adverse effects of RETIN-A have been reversible upon discontinuance of therapy (see Dosage and Administration Section).

OVERDOSAGE

If medication is applied excessively, no more rapid or better results will be obtained and marked redness, peeling, or discomfort may occur. Oral ingestion of the drug may lead to the same side effects as those associated with excessive oral intake of Vitamin A

DOSAGE AND ADMINISTRATION

RETIN-A Gel, Cream or Liquid should be applied once a day, before retiring, to the skin where acne lesions appear, using enough to cover the entire affected area lightly. Liquid: The liquid may be applied using a fingertip, gauze pad, or cotton swab. If gauze or cotton is employed, care should be taken not to oversaturate it to the extent that the liquid would run into areas where treatment is not intended. Gel: Excessive application results in “pilling” of the gel, which minimizes the likelihood of over application by the patient.

Application may cause a transitory feeling of warmth or slight stinging. In cases where it has been necessary to temporarily discontinue therapy or to reduce the frequency of application, therapy may be resumed or frequency of application increased when the patients become able to tolerate the treatment.

Alterations of vehicle, drug concentration, or dose frequency should be closely monitored by careful observation of the clinical therapeutic response and skin tolerance.

During the early weeks of therapy, an apparent exacerbation of inflammatory lesions may occur. This is due to the action of the medication on deep, previously unseen lesions and should not be considered a reason to discontinue therapy.

Therapeutic results should be noticed after two to three weeks but more than six weeks of therapy may be required before definite beneficial effects are seen.

Once the acne lesions have responded satisfactorily, it may be possible to maintain the improvement with less frequent applications, or other dosage forms.

Patients treated with RETIN-A (tretinoin) acne treatment may use cosmetics, but the area to be treated should be cleansed thoroughly before the medication is applied. (See Precautions.)

HOW SUPPLIED

RETIN-A (tretinoin) is supplied as:

RETIN-A Cream
 | RETIN-A | RETIN-A
NDC Code | Strength/Form | Quantity
54868-1760-1 | 0.025% | Cream - 20g
54868-1760-2 | 0.025% | Cream - 45g
54868-0267-1 | 0.05% | Cream - 20g
54868-0267-2 | 0.05% | Cream - 45g
54868-0268-1 | 0.1% | Cream - 20g
54868-0268-2 | 0.1% | Cream - 45g
RETIN-A Gel
54868-0269-2 | 0.01% | Gel - 15g
54868-0270-1 | 0.025% | Gel - 45g

Storage Conditions: RETIN-A Liquid, 0.05%, and RETIN-A Gel, 0.025% and 0.01%: store below 86°F. RETIN-A Cream, 0.1%, 0.05%, and 0.025%: store below 80°F.

ORTHO DERMATOLOGICAL

Division of Ortho-McNeil

Pharmaceutical, Inc.

Skillman, New Jersey 08558

©OMP 2001 Revised February 2001 Printed in U.S.A. 643-10-490-9

PATIENT INSTRUCTIONS

Retin-A®
(tretinoin)

Acne Treatment

IMPORTANT

Read Directions Carefully Before Using

Cream · Gel · Liquid

For Topical Use Only

THIS LEAFLET TELLS YOU ABOUT RETIN-A (TRETINOIN) ACNE TREATMENT AS PRESCRIBED BY YOUR PHYSICIAN. THIS PRODUCT IS TO BE USED ONLY ACCORDING TO YOUR DOCTOR'S INSTRUCTIONS, AND IT SHOULD NOT BE APPLIED TO OTHER AREAS OF THE BODY OR TO OTHER GROWTHS OR LESIONS. THE LONG-TERM SAFETY AND EFFECTIVENESS OF THIS PRODUCT IN OTHER DISORDERS HAVE NOT BEEN EVALUATED. IF YOU HAVE ANY QUESTIONS, BE SURE TO ASK YOUR DOCTOR.

WARNINGS AND PRECAUTIONS

The effects of the sun on your skin. As you know, overexposure to natural sunlight or the artificial sunlight of a sunlamp can cause sunburn. Overexposure to the sun over many years may cause premature aging of the skin and even skin cancer. The chance of these effects occurring will vary depending on skin type, the climate and the care taken to avoid overexposure to the sun. Therapy with RETIN-A may make your skin more susceptible to sunburn and other adverse effects of the sun, so unprotected exposure to natural or artificial sunlight should be minimized.

Laboratory findings. When laboratory mice are exposed to artificial sunlight, they often develop skin tumors. These sunlight-induced tumors may appear more quickly and in greater number if the mouse is also topically treated with the active ingredient in RETIN-A, tretinoin. In some studies, under different conditions, however, when mice treated with tretinoin were exposed to artificial sunlight, the incidence and rate of development of skin tumors was reduced. There is no evidence to date that tretinoin alone will cause the development of skin tumors in either laboratory animals or humans. However, investigations in this area are continuing.

Use caution in the sun. When outside, even on hazy days, areas treated with RETIN-A should be protected. An effective sunscreen should be used any time you are outside (consult your physician for a recommendation of an SPF level which will provide you with the necessary high level of protection). For extended sun exposure, protective clothing, like a hat, should be worn. Do not use artificial sunlamps while you are using RETIN-A. If you do become sunburned, stop your therapy with RETIN-A until your skin has recovered.

Avoid excessive exposure to wind or cold. Extremes of climate tend to dry or burn normal skin. Skin treated with RETIN-A may be more vulnerable to these extremes. Your physician can recommend ways to manage your acne treatment under such conditions.

Possible problems. The skin of certain sensitive individuals may become excessively red, swollen, blistered or crusted. If you are experiencing severe or persistent irritation, discontinue the use of RETIN-A and consult your physician.

There have been reports that, in some patients, areas treated with RETIN-A developed a temporary increase or decrease in the amount of skin pigment (color) present. The pigment in these areas returned to normal either when the skin was allowed to adjust to RETIN-A or therapy was discontinued.

Use other medication only on your physician's advice. Only your physician knows which other medications may be helpful during treatment and will recommend them to you if necessary. Follow the physician's instructions carefully. In addition, you should avoid preparations that may dry or irritate your skin. These preparations may include certain astringents, toiletries containing alcohol, spices or lime, or certain medicated soaps, shampoos and hair permanent solutions. Do not allow anyone else to use this medication.

Do not use other medications with RETIN-A which are not recommended by your doctor. The medications you have used in the past might cause unnecessary redness or peeling.

If you are pregnant, think you are pregnant or are nursing an infant: No studies have been conducted in humans to establish the safety of RETIN-A in pregnant women. If you are pregnant, think you are pregnant, or are nursing a baby, consult your physician before using this medication.

GELS ARE FLAMMABLE. Note: Keep away from heat and flame. Keep tube tightly closed.

AND WHILE YOU'RE ON RETIN-A THERAPY

Use a mild, non-medicated soap. Avoid frequent washings and harsh scrubbing. Acne isn't caused by dirt, so no matter how hard you scrub, you can't wash it away. Washing too frequently or scrubbing too roughly may at times actually make your acne worse. Wash your skin gently with a mild, bland soap. Two or three times a day should be sufficient. Pat skin dry with a towel. Let the face dry 20 to 30 minutes before applying RETIN-A. Remember, excessive irritation such as rubbing, too much washing, use of other medications not suggested by your physician, etc., may worsen your acne.

HOW TO USE RETIN-A (TRETINOIN)

To get the best results with RETIN-A therapy, it is necessary to use it properly. Forget about the instructions given for other products and the advice of friends. Just stick to the special plan your doctor has laid out for you and be patient. Remember, when RETIN-A is used properly, many users see improvement by 12 weeks. AGAIN, FOLLOW INSTRUCTIONS – BE PATIENT – DON'T START AND STOP THERAPY ON YOUR OWN – IF YOU HAVE QUESTIONS, ASK YOUR DOCTOR.

To help you use the medication correctly, keep these simple instructions in mind.

- Apply RETIN-A once daily before bedtime, or as directed by your physician. Your physician may advise, especially if your skin is sensitive, that you start your therapy by applying RETIN-A every other night. First, wash with a mild soap and dry your skin gently.WAIT 20 to 30 MINUTES BEFORE APPLYING MEDICATION; it is important for skin to be completely dry in order to minimize possible irritation.
- It is better not to use more than the amount suggested by your physician or to apply more frequently than instructed.Too much may irritate the skin, waste medication and won't give faster or better results.
- Keep the medication away from the corners of the nose, mouth, eyes and open wounds. Spread away from these areas when applying.
- Cream: Squeeze about a half inch or less of medication onto the fingertip. While that should be enough for your whole face, after you have some experience with the medication you may find you need slightly more or less to do the job. The medication should become invisible almost immediately. If it is still visible, you are using too much. Cover the affected area lightly with RETIN-A (tretinoin) Cream by first dabbing it on your forehead, chin and both cheeks, then spreading it over the entire affected area. Smooth gently into the skin.
- Gel: Squeeze about a half inch or less of medication onto the fingertip. While that should be enough for your whole face, after you have some experience with the medication you may find you need slightly more or less to do the job. The medication should become invisible almost immediately. If it is still visible, or if dry flaking occurs from the gel within a minute or so, you are using too much. Cover the affected area lightly with RETIN-A (tretinoin) Gel by first dabbing it on your forehead, chin and both cheeks, then spreading it over the entire affected area. Smooth gently into the skin.
- Liquid: RETIN-A (tretinoin) Liquid may be applied to the skin where acne lesions appear, spreading the medication over the entire affected area, using a fingertip, gauze pad, or cotton swab. If gauze or cotton is employed, care should be taken not to oversaturate it to the extent that the liquid would run into areas where treatment is not intended (such as corners of the mouth, eyes, and nose).
- It is recommended that you apply a moisturizer or a moisturizer with sunscreen that will not aggravate your acne (noncomedogenic) every morning after you wash.

WHAT TO EXPECT WITH YOUR NEW TREATMENT

RETIN-A works deep inside your skin and this takes time. You cannot make RETIN-A work any faster by applying more than one dose each day, but an excess amount of RETIN-A may irritate your skin. Be patient.

There may be some discomfort or peeling during the early days of treatment. Some patients also notice that their skin begins to take on a blush.

These reactions do not happen to everyone. If they do, it is just your skin adjusting to RETIN-A and this usually subsides within two to four weeks. These reactions can usually be minimized by following instructions carefully. Should the effects become excessively troublesome, consult your doctor.

BY THREE TO SIX WEEKS, some patients notice an appearance of new blemishes (papules and pustules). At this stage it is important to continue using RETIN-A.

If RETIN-A is going to have a beneficial effect for you, you should notice a continued improvement in your appearance after 6 to 12 weeks of therapy. Don't be discouraged if you see no immediate improvement. Don't stop treatment at the first signs of improvement.

Once your acne is under control you should continue regular application of RETIN-A until your physician instructs otherwise.

IF YOU HAVE QUESTIONS

All questions of a medical nature should be taken up with your doctor. For more information about RETIN-A (tretinoin), call our toll-free number: 800-426-7762. Call between 9:00 a.m. and 3:00 p.m. Eastern Time, Monday through Friday.

ORTHO DERMATOLOGICAL

Division of Ortho-McNeil

Pharmaceutical, Inc.

Skillman, New Jersey 08558

©OMP 2001 Revised February 2001 Printed in U.S.A. 643-10-490-9

PRINCIPAL DISPLAY PANEL

Retin-A®
(tretinoin)

0.025% Cream

Retin-A®
(tretinoin)

0.025% Gel

Retin-A®
(tretinoin)

0.05% Cream

Retin-A®
(tretinoin)

0.1% Cream

Retin-A®
(tretinoin)

0.1% Gel